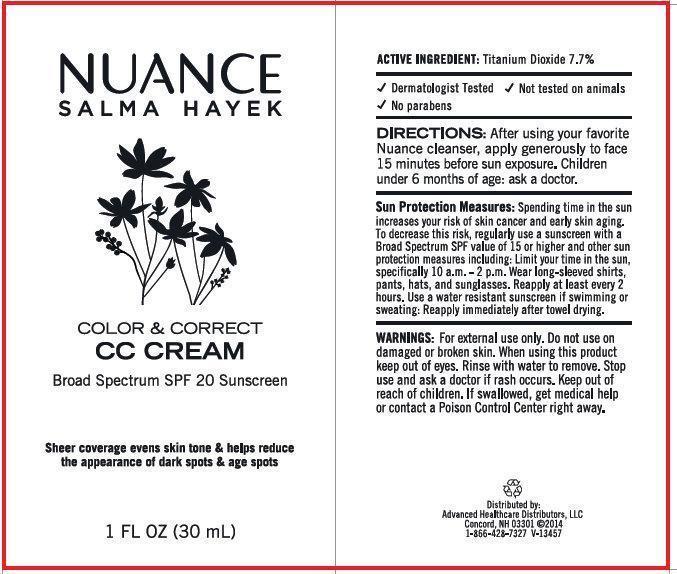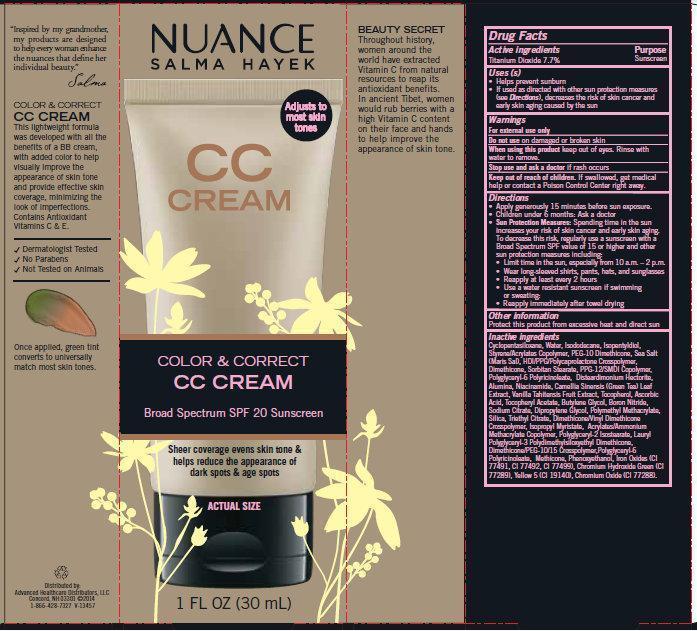 DRUG LABEL: NUANCE SALMA HAYAK Color and Correct CC Cream Broad Spectrum SPF 20 Sunscreen
NDC: 59779-505 | Form: CREAM
Manufacturer: CVS Pharmacy
Category: otc | Type: HUMAN OTC DRUG LABEL
Date: 20141028

ACTIVE INGREDIENTS: TITANIUM DIOXIDE 77 mg/1 mL
INACTIVE INGREDIENTS: CYCLOMETHICONE 5; WATER; ISODODECANE; ISOPENTYLDIOL; SEA SALT; DIMETHICONE; SORBITAN MONOSTEARATE; PPG-12/SMDI COPOLYMER; DISTEARDIMONIUM HECTORITE; ALUMINUM OXIDE; NIACINAMIDE; GREEN TEA LEAF; VANILLA; TOCOPHEROL; ASCORBIC ACID; .ALPHA.-TOCOPHEROL ACETATE; BUTYLENE GLYCOL; BORON NITRIDE; SODIUM CITRATE; DIPROPYLENE GLYCOL; SILICON DIOXIDE; TRIETHYL CITRATE; ISOPROPYL MYRISTATE; POLYGLYCERYL-2 MONOISOSTEARATE; PHENOXYETHANOL; FERRIC OXIDE RED; FERROSOFERRIC OXIDE; CHROMIUM HYDROXIDE GREEN; FD&C YELLOW NO. 5; CHROMIC OXIDE

NUANCE SALMA HAYAK Color and Correct CC Cream Broad Spectrum SPF 20 Sunscreen

Active ingredients

Titanium Dioxide 7.7%

Purpose

Sunscreen

Use (s)

• Helps prevent sunburn
• If used as directed with other sun protection measures (see Directions), decreases the risk of skin cancer and early skin aging caused by the sun

Warnings

For external use only

Do not use

on damaged or broken skin

When using this product

keep out of eyes. Rinse with water to remove.

Stop use and ask a doctor

if rash occurs

Keep out of reach of children.

If swallowed, get medical help or contact a Poison Control Center right away.

Directions

• Apply generously 15 minutes before sun exposure.
• Children under 6 months: Ask a doctor
• Sun Protection Measures: Spending time in the sun increases your risk of skin cancer and early skin aging. To decrease this risk, regularly use a sunscreen with a Broad Spectrum SPF value of 15 or higher and other sun protection measures including:
• Limit time in the sun, especially from 10 a.m. – 2 p.m.
• Wear long-sleeved shirts, pants, hats, and sunglasses
• Reapply at least every 2 hours
• Use a water resistant sunscreen if swimming or sweating:
• Reapply immediately after towel drying

Other information

Protect this product from excessive heat and direct sun

Inactive ingredients

Cyclopentasiloxane, Water, Isododecane, Isopentyldiol, Styrene/Acrylates Copolymer, PEG-10 Dimethicone, Sea Salt (Maris Sal), HDI/PPG/Polycaprolactone Crosspolymer, Dimethicone, Sorbitan Stearate, PPG-12/SMDI Copolymer, Polyglyceryl-6 Polyricinoleate, Disteardimonium Hectorite, Alumina, Niacinamide, Camellia Sinensis (Green Tea) Leaf Extract, Vanilla Tahitensis Fruit Extract, Tocopherol, Ascorbic Acid, Tocopheryl Acetate, Butylene Glycol, Boron Nitride, Sodium Citrate, Dipropylene Glycol, Polymethyl Methacrylate, Silica, Triethyl Citrate, Dimethicone/Vinyl Dimethicone Crosspolymer, Isopropyl Myristate, Acrylates/Ammonium Methacrylate Copolymer, Polyglyceryl-2 Isostearate, Lauryl Polyglyceryl-3 Polydimethylsiloxyethyl Dimethicone, Dimethicone/PEG-10/15 Crosspolymer,Polyglyceryl-6 Polyricinoleate, Methicone, Phenoxyethanol, Iron Oxides (CI 77491, CI 77492, CI 77499), Chromium Hydroxide Green (CI 77289), Yellow 5 (CI 19140), Chromium Oxide (CI 77288).

NUANCE SALMA HAYEK

"Inspired by my grandmother, my products are designed to help every woman enhance the nuances that define her individual beauty." Salma COLOR and CORRECT CC CREAM This lightweight formula was developed with all the benefits of a BB cream, with added color to help visually improve the appearance of skin tone and provide effective skin coverage, minimizing the look of imperfections. Contains Antioxidant Vitamins C and E. Dermatologist Tested No Parabens Not Tested on Animals Once applied, green tint converts to universally match most skin tones. BEAUTY SECRET Throughout history, women around the world have extracted Vitamin C from natural resources to reap its antioxidant benefits. In ancient Tibet, women would rub berries with a high Vitamin C content on their face and hands to help improve the appearance of skin tone.